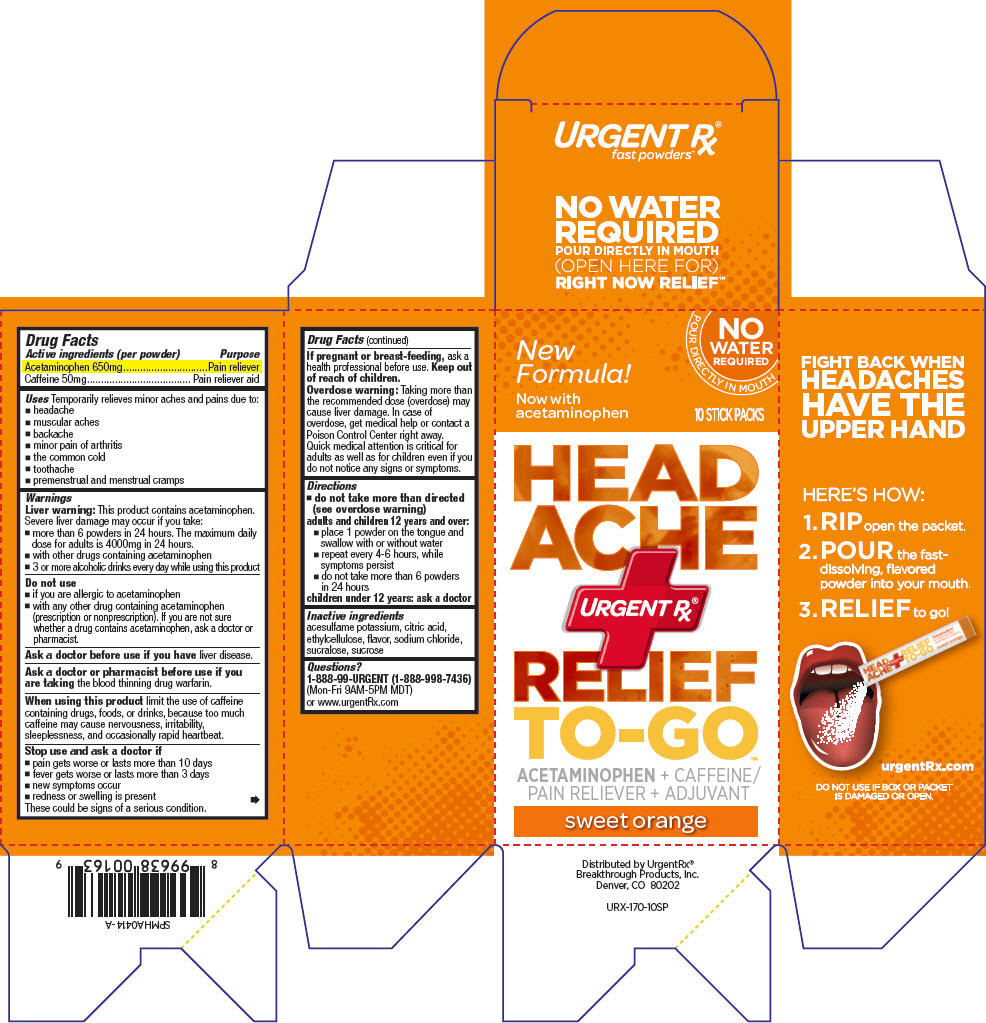 DRUG LABEL: Headache Relief To Go
NDC: 51596-011 | Form: POWDER
Manufacturer: Breakthrough Products Inc.
Category: otc | Type: HUMAN OTC DRUG LABEL
Date: 20140616

ACTIVE INGREDIENTS: acetaminophen 650 mg/1 1; caffeine 50 mg/1 1
INACTIVE INGREDIENTS: acesulfame potassium; citric acid monohydrate; ethylcelluloses; sodium chloride; sucralose; sucrose

Headache Relief To Go™

Drug Facts

ACTIVE INGREDIENT

Active ingredients (per powder) | Purpose
Acetaminophen 650 mg | Pain reliever
Caffeine 50 mg | Pain reliever aid

Uses

Temporarily relieves minor aches and pains due to:

- headache
- muscular aches
- backache
- minor pain of arthritis
- the common cold
- toothache
- premenstrual and menstrual cramps

Warnings

Liver warning

This product contains acetaminophen. Severe liver damage may occur if you take:

- more than 6 powders in 24 hours. The maximum daily dose for adults is 4000mg in 24 hours.
- with other drugs containing acetaminophen
- 3 or more alcoholic drinks every day while using this product

Do not use

- if you are allergic to acetaminophen
- with any other drug containing acetaminophen (prescription or nonprescription). If you are not sure whether a drug contains acetaminophen, ask a doctor or pharmacist.

Ask a doctor before use if you have liver disease

Ask a doctor or pharmacist before use if you are taking the blood thinning drug warfarin

When using this product limit the use of caffeine containing drugs, foods, or drinks, because too much caffeine may cause nervousness, irritability, sleeplessness, and occasionally rapid heartbeat.

Stop use and ask a doctor if

- pain gets worse or lasts for more than 10 days
- fever gets worse or lasts for more than 3 days
- new symptoms occur
- redness or swelling is present

These could be signs of a serious condition.

PREGNANCY OR BREAST FEEDING

If pregnant or breast-feeding, ask a health professional before use.

Keep out of reach of children.

Overdose warning

Taking more than the recommended dose (overdose) may cause liver damage. In case of overdose, get medical help or contact a Poison Control Center right away. Quick medical attention is critical for adults as well as for children even if you do not notice any signs or symptoms.

Directions

- do not take more than directed (see overdose warning)

adults and children 12 years and over:

- place 1 powder on the tongue and swallow with or without water
- repeat every 4-6 hours, wile symptoms persist
- do not take more than 6 pouches in 24 hours

children under 12 years: ask a doctor

Inactive ingredients

acesulfame potassium, citric acid, ethylcellulose, flavor, sodium chloride, sucralose, sucrose

Questions?

1-888-99-URGENT (1-888-998-7436) (Mon-Fri 9AM-5PM MDT) or www.urgentRx.com

DO NOT USE IF BOX OR PACKET
IS DAMAGED OR OPEN

Distributed by UrgentRx®
Breakthrough Products, Inc.
Denver, CO 80202

PRINCIPAL DISPLAY PANEL - 10 Packet Box

New
Formula!

Now with
acetaminophen
NO WATER REQUIRED
POUR DIRECTLY IN MOUTH

10 STICK PACKS

HEADACHE

URGENTRX

RELEIF

TO-GO

ACETAMINOPHEN + CAFFEINE/
PAIN RELIEVER + ADJUVANT

sweet orange